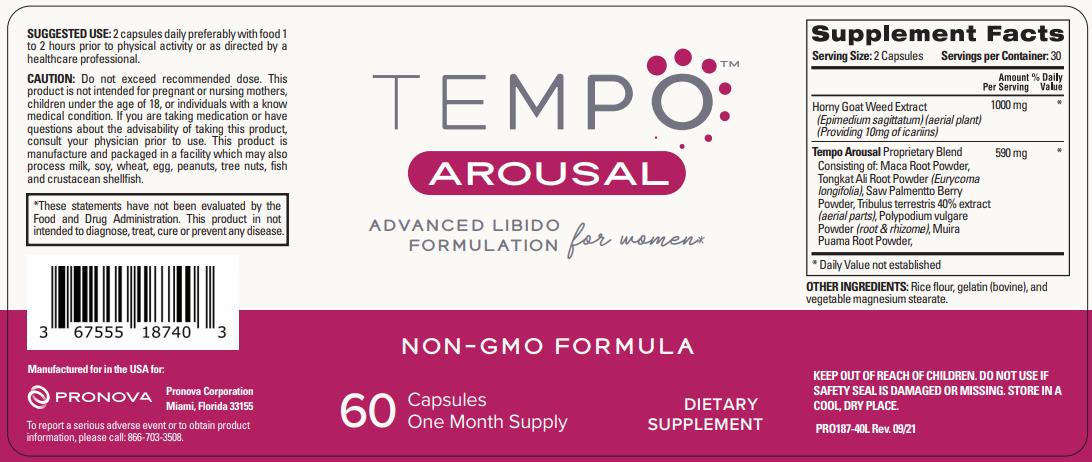 DRUG LABEL: TEMPO AROUSAL
NDC: 67555-188 | Form: CAPSULE
Manufacturer: Pronova Corporation
Category: other | Type: DIETARY SUPPLEMENT
Date: 20230424

ACTIVE INGREDIENTS: EPIMEDIUM SAGITTATUM TOP 1000 mg/1 1; LEPIDIUM MEYENII ROOT 100 mg/1 1; EURYCOMA LONGIFOLIA ROOT 100 mg/1 1; SAW PALMETTO 100 mg/1 1; TRIBULUS TERRESTRIS FLOWER 100 mg/1 1; POLYPODIUM VIRGINIANUM ROOT 100 mg/1 1; PTYCHOPETALUM OLACOIDES ROOT 90 mg/1 1
INACTIVE INGREDIENTS: BROWN RICE; GELATIN TYPE B BOVINE (230 BLOOM); MAGNESIUM STEARATE

TEMPOTM AROUSAL

STATEMENT OF IDENTITY

Supplement Facts
Serving Size: 2 Capsules Servings per Container: 30
 | Amount; Per Serving | % Daily; Value
Horny Goat Weed Extract; (Epimedium sagittatum) (aerial plant); (Providing 10mg of icariins) | 1000 mg | *
Tempo Arousal Proprietary Blend; Consisting of: Maca Root Powder, Tongkat Ali Root Powder (Eurycoma longifolia), Saw Palmetto Berry; Powder, Tribulus terrestris 40% extract (aerial parts), Polypodium vulgare; Powder (root & rhizome), Muira; Puama Root Powder | 590 mg | *
* Daily Value not established

OTHER INGREDIENTS: Rice flour, gelatin (bovine), and vegetable magnesium stearate

KEEP OUT OF REACH OF CHILDREN. DO NOT USE IF SAFETY SEAL IS DAMAGED OR MISSING. STORE IN A COOL, DRY PLACE.

DOSAGE AND ADMINISTRATION

SUGGESTED USE: 2 capsules daily preferably with food 1 to 2 hours prior to physical activity or as directed by a healthcare professional.

PRECAUTIONS

CAUTION: Do not exceed recommended dose. This product is not intended for pregnant or nursing mothers, children under the age of 18, or individuals with a known medical condition. If you are taking medication or have questions about the advisability of taking this product, consult your physician prior to use. This product is manufacture and packaged in a facility which may also process milk, soy, wheat, egg, peanuts, tree nuts, fish and crustacean shellfish.

*These statements have not been evaluated by the Food and Drug Administration. This product in not intended to diagnose, treat, cure or prevent any disease.

Manufactured for in the USA for:

Pronova Corporation
Miami, Florida 33155

To report a serious adverse event or to obtain product information, please call: 866-703-3508.

HEALTH CLAIM

ADVANCED LIBIDO FORMULATION for women*

NON-GMO FORMULA

DIETARY SUPPLEMENT

One Month Supply